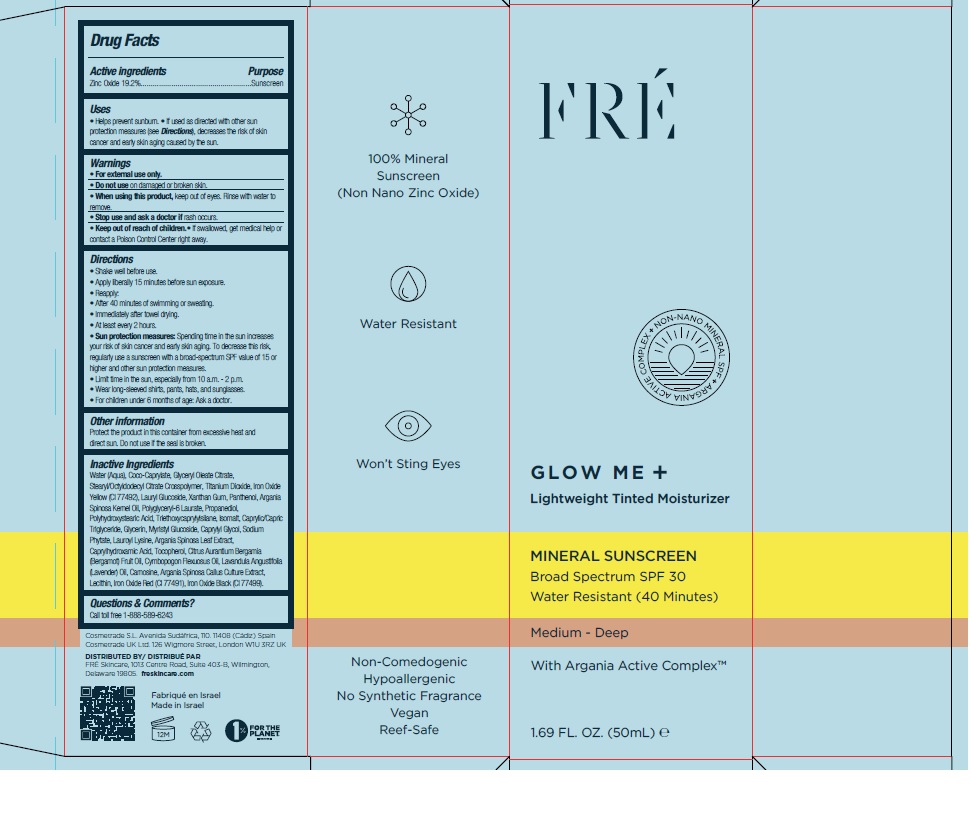 DRUG LABEL: Fre Glow Me Lightweight Tinted Moisturizer Medium Deep
NDC: 69435-1402 | Form: CREAM
Manufacturer: Peer Pharm Ltd.
Category: otc | Type: HUMAN OTC DRUG LABEL
Date: 20250213

ACTIVE INGREDIENTS: ZINC OXIDE 19.2 g/100 mL
INACTIVE INGREDIENTS: WATER; COCO-CAPRYLATE; GLYCERYL MONOOLEATE CITRATE; STEARYL/OCTYLDODECYL CITRATE CROSSPOLYMER; LAURYL GLUCOSIDE; XANTHAN GUM; PANTHENOL; PROPANEDIOL; POLYHYDROXYSTEARIC ACID (2300 MW); TRIETHOXYCAPRYLYLSILANE; ISOMALT; MEDIUM-CHAIN TRIGLYCERIDES; GLYCERIN; MYRISTYL GLUCOSIDE; CAPRYLYL GLYCOL; PHYTATE SODIUM; LAUROYL LYSINE; ARGANIA SPINOSA LEAF; CAPRYLHYDROXAMIC ACID; TOCOPHEROL; BERGAMOT OIL; EAST INDIAN LEMONGRASS OIL; LAVENDER OIL; CARNOSINE; ARGAN OIL; LECITHIN, SOYBEAN; TITANIUM DIOXIDE; FERRIC OXIDE YELLOW; FERRIC OXIDE RED; FERROSOFERRIC OXIDE

FRE GLOW ME Lightweight Tinted Moisturizer SPF 30 - Medium -Deep

Active Ingredients

Zinc Oxide 19.2%

Purpose

Sunscreen

Uses

- Helps prevent sunburn
- if used as directed with other sun protection measures (see Directions), decreases the risk of skin cancer and early skin aging caused by the sun.

Warnings

- For external use only
- Do not use on damaged or broken skin.
- When using this product, Keep out of eyes. Rinse with water to remove.
- Stop use and ask a doctor if rash occurs

Keep out of reach of children.

If swallowed, call a Poison Control Center or get medical help right away.

Directions

• Shake well before use

- Apply liberally 15 minutes before sun exposure
- Reapply:
- After 80 minutes of swimming or sweating
- Immediately after towel drying
- At least every 2 hours
- Sun Protection MeasuresSpending time in the sun increases your risk of skin cancer and early skin aging. To decrease this risk, regularly use a sunscreen with a broad-spectrum SPF value of 15 or higher and other sun protection measures including:
- limit time in the sun, especially from 10a.m. to 2p.m.
- Wear long-sleeve shirts, pants, hats, and sunglasses.
- Children under 6 months: ask a doctor

Other information

Protect the product in this container from excessive heat and direct sun. Do not use if the seal is broken.

Inactive Ingredients

Water (Aqua), Coco-Caprylate, Glyceryl Oleate Citrate,Stearyl/Octyldodecyl Citrate Crosspolymer, Titanium Dioxide, Iron Oxide Yellow (CI 77492), Lauryl Glucoside, Xanthan Gum, Panthenol, Argania Spinosa Kernel Oil, Polyglyceryl-6 Laurate, Propanediol,Polyhydroxystearic Acid, Triethoxycaprylylsilane, Isomalt, Caprylic/Capric Triglyceride, Glycerin, Myristyl Glucoside, Caprylyl Glycol, Sodium Phytate, Lauroyl Lysine, Argania Spinosa Leaf Extract, Caprylhydroxamic Acid, Tocopherol, Citrus Aurantium Bergamia(Bergamot) Fruit Oil, Cymbopogon Flexuosus Oil, Lavandula Angustifolia(Lavender) Oil, Carnosine, Argania Spinosa Callus Culture Extract,Lecithin, Iron Oxide Red (CI 77491), Iron Oxide Black (CI 77499).

Questions or Comments

Call toll free 1-888-589-6243